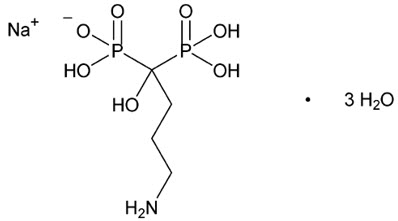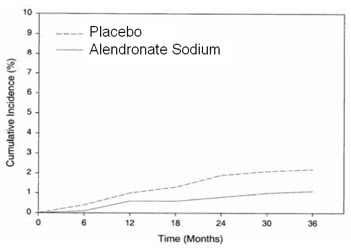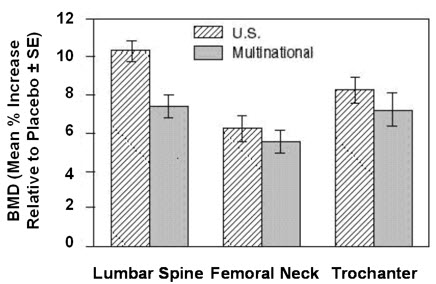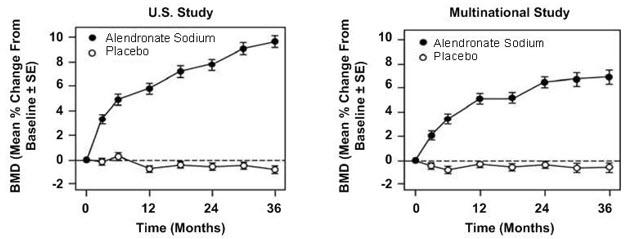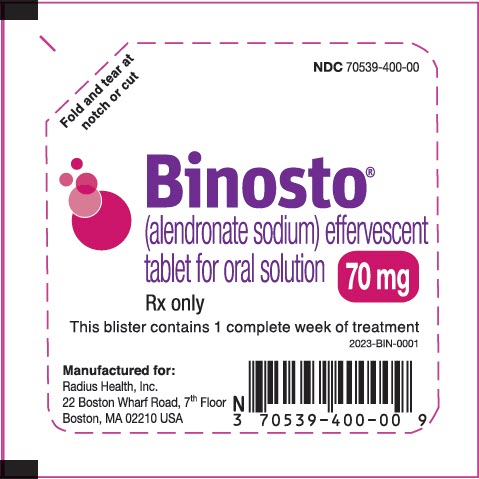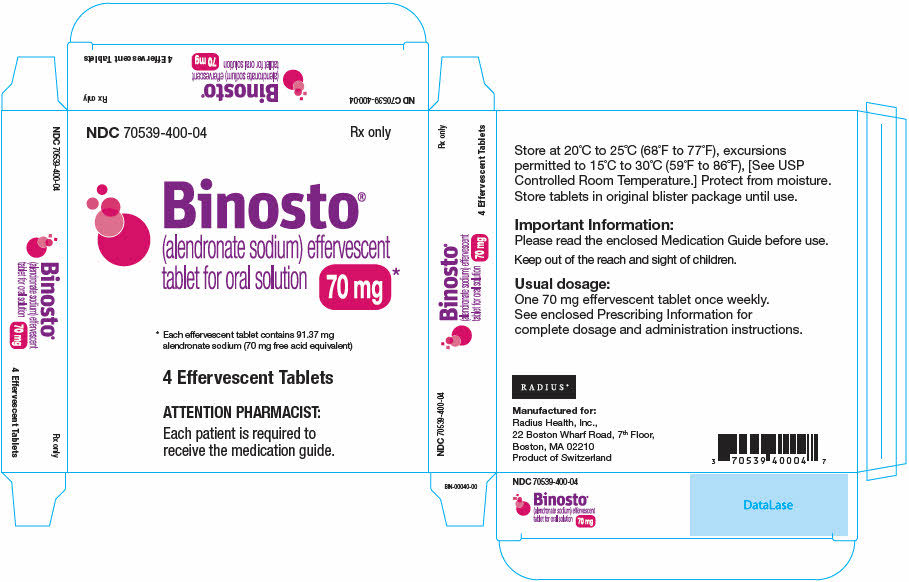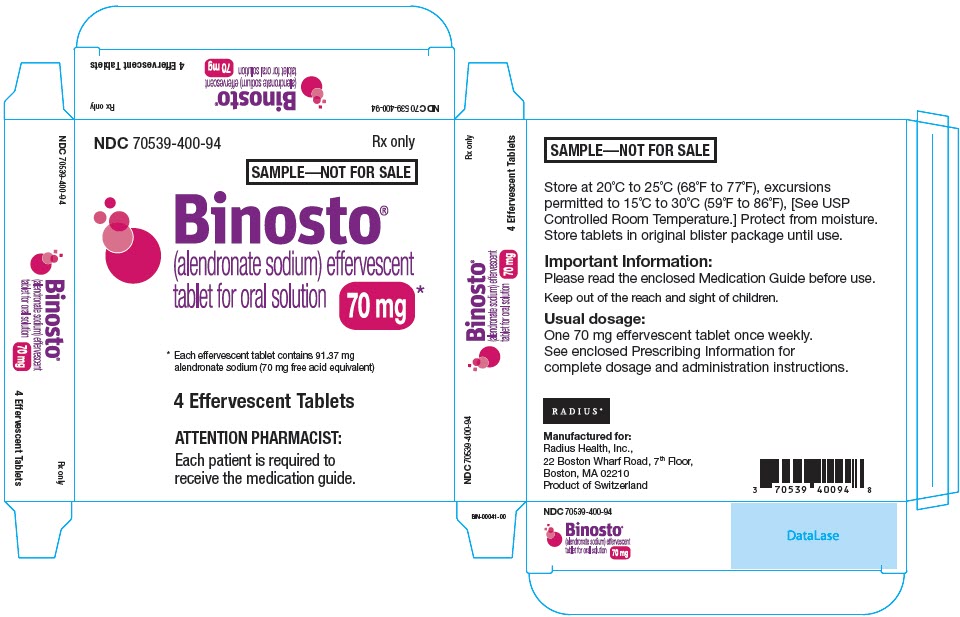 DRUG LABEL: Binosto
NDC: 70539-400 | Form: TABLET, EFFERVESCENT
Manufacturer: Radius Health, Inc.
Category: prescription | Type: HUMAN PRESCRIPTION DRUG LABEL
Date: 20260206

ACTIVE INGREDIENTS: ALENDRONATE SODIUM 91.37 mg/1 1
INACTIVE INGREDIENTS: MONOSODIUM CITRATE 1900 mg/1 1; ANHYDROUS CITRIC ACID 839.63 mg/1 1; SODIUM BICARBONATE 751 mg/1 1; SODIUM CARBONATE 430 mg/1 1; WATER

HIGHLIGHTS OF PRESCRIBING INFORMATION

These highlights do not include all the information needed to use BINOSTO® safely and effectively. See full prescribing information for BINOSTO.
BINOSTO (alendronate sodium) effervescent tablets for oral solution
Initial U.S. Approval: 1995

RECENT MAJOR CHANGES

- Warnings and Precautions, Atypical Fractures Including Femoral Fractures (5.5) | 02/2026

1 INDICATIONS AND USAGE

BINOSTO is a bisphosphonate indicated for:

- Treatment of osteoporosis in postmenopausal women (1.1)
- Treatment to increase bone mass in men with osteoporosis (1.2)

Limitation of use: Optimal duration of use has not been determined. For patients at low-risk for fracture, consider drug discontinuation after 3 to 5 years of use (1.3)

2 DOSAGE AND ADMINISTRATION

- 70 mg BINOSTO effervescent tablet once weekly. (2.1, 2.2)
- Instruct patients to: (2.3)
  - Dissolve one tablet of BINOSTO in approximately half a glass of plain room temperature water (4 oz). Wait at least 5 minutes after the effervescence stops, stir the solution for approximately 10 seconds and consume contents.
  - Swallow solution at least 30 minutes before the first food, beverage, or medication of the day.
  - Avoid lying down for at least 30 minutes after taking BINOSTO and until after the first food of the day.

3 DOSAGE FORMS AND STRENGTHS

Effervescent tablets, 70 mg (3)

4 CONTRAINDICATIONS

- Abnormalities of the esophagus which delay emptying such as stricture or achalasia (4, 5.1)
- Inability to stand/sit upright for at least 30 minutes (4, 5.1)
- Increased risk of aspiration. (4)
- Hypocalcemia (4, 5.2)
- Hypersensitivity to any component of this product (4, 6.2)

5 WARNINGS AND PRECAUTIONS

- Upper Gastrointestinal Adverse Reactions can occur. Instruct patients to follow dosing instructions. Discontinue if new or worsening symptoms occur. (5.1)
- Hypocalcemia can worsen and must be corrected prior to use. (5.2)
- Severe Bone, Joint, Muscle Pain may occur. Discontinue use if severe symptoms develop. (5.3)
- Osteonecrosis of the Jaw has been reported. (5.4)
- Atypical Fractures Including Femoral Fractures have been reported. Patients with new thigh or groin pain should be evaluated to rule out a femoral fracture. Risk/benefit of continuing bisphosphonate therapy should be re-evaluated in these patients and interruption of bisphosphonate therapy should be considered. (5.5)
- Sodium Content: Each tablet contains 603 mg sodium, equivalent to 1532 mg NaCl. Use caution in patients on sodium restriction. (5.7)

6 ADVERSE REACTIONS

The most common adverse reactions (incidence greater than or equal to 3%) are abdominal pain, acid regurgitation, constipation, diarrhea, dyspepsia, musculoskeletal pain, and nausea. (6.1)

To report SUSPECTED ADVERSE REACTIONS, contact Radius Health, Inc. at 1-855-672-3487 or FDA at 1-800-FDA-1088 or www.fda.gov/medwatch

7 DRUG INTERACTIONS

- Calcium supplements, antacids or oral medications containing multivalent cations interfere with absorption of alendronate. (7.1)
- Use caution when co-prescribing aspirin/nonsteroidal anti- inflammatory drugs that may worsen gastrointestinal irritation. (7.2, 7.3)

8 USE IN SPECIFIC POPULATIONS

- Pregnancy: Discontinue when pregnancy is recognized. (8.1)
- BINOSTO is not indicated for use in pediatric patients. (8.4)
- BINOSTO is not recommended in patients with renal impairment (creatinine clearance less than 35 mL/min). (5.6, 8.6)

FULL PRESCRIBING INFORMATION

1 INDICATIONS AND USAGE

1.1 Treatment of Osteoporosis in Postmenopausal Women

BINOSTO effervescent tablet 70 mg is indicated for the treatment of osteoporosis in postmenopausal women. For the treatment of osteoporosis, alendronate sodium increases bone mass and reduces the incidence of fractures, including those of the hip and spine (vertebral compression fractures). [See Clinical Studies (14.1).]

1.2 Treatment to Increase Bone Mass in Men With Osteoporosis

BINOSTO is indicated for treatment to increase bone mass in men with osteoporosis [see Clinical Studies (14.2)].

1.3 Important Limitations of Use

The optimal duration of use has not been determined. The safety and effectiveness of BINOSTO for the treatment of osteoporosis are based on clinical data of four years duration. All patients on bisphosphonate therapy should have the need for continued therapy re-evaluated on a periodic basis. Patients at low-risk for fracture should be considered for drug discontinuation after 3 to 5 years of use. Patients who discontinue therapy should have their risk for fracture re-evaluated periodically.

2 DOSAGE AND ADMINISTRATION

2.1 Treatment of Osteoporosis in Postmenopausal Women

The recommended dosage is one 70 mg effervescent tablet once weekly.

2.2 Treatment to Increase Bone Mass in Men With Osteoporosis

The recommended dosage is one 70 mg effervescent tablet once weekly.

2.3 Important Administration Instructions

Instruct patients to do the following to assure adequate drug absorption and to decrease the risk of esophageal adverse reactions:

- Take BINOSTO upon arising for the day and at least 30 minutes before the first food, beverage, or medication of the day.
- Patients should not swallow the undissolved effervescent tablet, should not chew the effervescent tablet or allow the effervescent tablet to dissolve in their mouths because of the risk for oropharyngeal irritation [see Warnings and Precautions (5.1)].
- Dissolve the effervescent tablet in 4 ounces room temperature plain water only (not mineral water or flavored water).
- Wait at least 5 minutes after the effervescence stops and then stir the buffered solution for approximately 10 seconds and ingest.
- Avoid lying down for at least 30 minutes after taking BINOSTO and until after their first food of the day.
- Do not take BINOSTO at bedtime or before arising for the day.
  Failure to follow these instructions may increase the risk of esophageal adverse reactions [see Warnings and Precautions (5.1)].

2.4 Recommendations for Calcium and Vitamin D Supplementation

Instruct patients to take supplemental calcium and vitamin D if dietary intake is inadequate [see Warnings and Precautions (5.2)]. Patients at increased risk for vitamin D insufficiency (e.g., over the age of 70 years, nursing home-bound, or chronically ill) may need vitamin D supplementation. Patients with gastrointestinal malabsorption syndromes may require higher doses of vitamin D supplementation and measurement of 25-hydroxyvitamin D should be considered.

2.5 Administration Instructions for Missed Doses

If the once-weekly dose is missed, instruct patients to take one dose on the morning after they remember. They should not take 2 doses on the same day but should return to taking one dose once a week, as originally scheduled on their chosen day.

3 DOSAGE FORMS AND STRENGTHS

BINOSTO effervescent tablets are round, flat-faced, white to off-white tablets, 25 mm in diameter, with beveled edges, with "M" debossed on one side, containing 91.37 mg of alendronate sodium, which is equivalent to 70 mg of free alendronic acid. After dissolution the solution has a pH of 4.8-5.4.

4 CONTRAINDICATIONS

BINOSTO is contraindicated in patients with the following conditions:

- Abnormalities of the esophagus which delay esophageal emptying such as stricture or achalasia [see Warnings and Precautions (5.1)]
- Inability to stand or sit upright for at least 30 minutes [see Dosage and Administration (2.3); Warnings and Precautions (5.1)]

Do not administer BINOSTO to patients at increased risk of aspiration

- Hypocalcemia [see Warnings and Precautions (5.2)]
- Hypersensitivity to any component of this product. Hypersensitivity reactions including urticaria and angioedema have been reported [see Adverse Reactions (6.2)].

5 WARNINGS AND PRECAUTIONS

5.1 Upper Gastrointestinal Adverse Reactions

BINOSTO, like other bisphosphonates administered orally, may cause local irritation of the upper gastrointestinal mucosa. Because of these possible irritant effects and a potential for worsening of the underlying disease, caution should be used when BINOSTO is given to patients with active upper gastrointestinal problems (such as known Barrett's esophagus, dysphagia, other esophageal diseases, gastritis, duodenitis, or ulcers).

Esophageal adverse experiences, such as esophagitis, esophageal ulcers and esophageal erosions, occasionally with bleeding and rarely followed by esophageal stricture or perforation, have been reported in patients receiving treatment with oral bisphosphonates including alendronate sodium. In some cases these have been severe and required hospitalization. Physicians should therefore be alert to any signs or symptoms signaling a possible esophageal reaction and patients should be instructed to discontinue BINOSTO and seek medical attention if they develop dysphagia, odynophagia, retrosternal pain or new or worsening heartburn.

The risk of severe esophageal adverse experiences appears to be greater in patients who lie down after taking oral bisphosphonates including alendronate sodium, and/or who continue to take oral bisphosphonates including alendronate sodium after developing symptoms suggestive of esophageal irritation. Therefore, it is very important that the full dosing instructions are provided to, and understood by, the patient [see Dosage and Administration (2.3)]. In patients who cannot comply with dosing instructions due to mental disability, therapy with BINOSTO should be used under appropriate supervision.

There have been post-marketing reports of gastric and duodenal ulcers with oral bisphosphonate use, some severe and with complications, although no increased risk was observed in controlled clinical trials [see Adverse Reactions (6.2)].

5.2 Mineral Metabolism

Hypocalcemia must be corrected before initiating therapy with BINOSTO [see Contraindications (4)]. Other disorders affecting mineral metabolism (such as vitamin D deficiency) should also be effectively treated. In patients with these conditions, serum calcium and symptoms of hypocalcemia should be monitored during therapy with BINOSTO.

Presumably due to the effects of BINOSTO on increasing bone mineral, small, asymptomatic decreases in serum calcium and phosphate may occur. Patients should receive adequate calcium and vitamin D intake.

5.3 Musculoskeletal Pain

In post-marketing experience, severe and occasionally incapacitating bone, joint, and/or muscle pain has been reported in patients taking bisphosphonates that are approved for the treatment of osteoporosis [see Adverse Reactions (6.2)]. This category of drugs includes BINOSTO. Most of the patients were postmenopausal women. The time to onset of symptoms varied from one day to several months after starting the drug. Discontinue use if severe symptoms develop. Most patients had relief of symptoms after stopping. A subset had recurrence of symptoms when rechallenged with the same drug or another bisphosphonate.

In placebo-controlled clinical studies of alendronate sodium, the percentages of patients with these symptoms were similar in the alendronate sodium and placebo groups.

5.4 Osteonecrosis of the Jaw

Osteonecrosis of the jaw (ONJ), which can occur spontaneously, is generally associated with tooth extraction and/or local infection with delayed healing, and has been reported in patients taking bisphosphonates, including alendronate sodium. Known risk factors for osteonecrosis of the jaw include invasive dental procedures (e.g., tooth extraction, dental implants, boney surgery), diagnosis of cancer, concomitant therapies (e.g., chemotherapy, corticosteroids, angiogenesis inhibitors), poor oral hygiene, and co-morbid disorders (e.g., periodontal and/or other pre-existing dental disease, anemia, coagulopathy, infection, ill-fitting dentures). The risk of ONJ may increase with duration of exposure to bisphosphonates.

For patients requiring invasive dental procedures, discontinuation of bisphosphonate treatment may reduce the risk for ONJ. Clinical judgment of the treating physician and/or oral surgeon should guide the management plan of each patient based on individual benefit/risk assessment.

Patients who develop osteonecrosis of the jaw while on bisphosphonate therapy should receive care by an oral surgeon. In these patients, extensive dental surgery to treat ONJ may exacerbate the condition. Discontinuation of bisphosphonate therapy should be considered based on individual benefit/risk assessment.

5.5 Atypical Fractures Including Femoral Fractures

Atypical, low-energy, or low trauma fractures of the femoral shaft have been reported during treatment with bisphosphonates, including alendronate sodium, in patients with osteoporosis. Atypical femur and other fractures most commonly occur with minimal or no trauma to the affected area. These fractures occurred anywhere in the femoral shaft from just below the lesser trochanter to above the supracondylar flare and are transverse or short oblique in orientation without evidence of comminution. Atypical fractures of other bones have also been reported. They may be bilateral. These fractures can also occur in osteoporotic patients who have not been treated with bisphosphonates. Concomitant treatment with glucocorticoids may also induce these fractures.

Prodromal pain in the affected area, usually presenting as dull, aching pain, weeks to months before a complete fracture occurs was reported by patients.

Any patient with a history of bisphosphonate exposure who presents with thigh or groin pain should be suspected of having an atypical fracture and should be evaluated to rule out an incomplete femur fracture. Bone pain in other locations should also be considered for evaluation of atypical fracture. Patients presenting with an atypical fracture should also be assessed for symptoms and signs of fracture in the contralateral limb. Risk/benefit of continuing bisphosphonate therapy should be re-evaluated in these patients and interruption of bisphosphonate therapy should be considered.

5.6 Renal Impairment

BINOSTO is not recommended for patients with creatinine clearance <35 mL/min.

5.7 Patients Sensitive to High Sodium Intake

Each BINOSTO effervescent tablet contains 603 mg of sodium, equivalent to approximately 1532 mg of salt (NaCl). Use caution in patients who must restrict their sodium intake, including some patients with a history of heart failure, hypertension, or other cardiovascular diseases [see Patient Counseling Information (17.3)].

6 ADVERSE REACTIONS

The following clinically significant adverse drug reactions are described elsewhere in the labeling:

- Upper Gastrointestinal Adverse Reactions [see Warnings and Precautions (5.1)]
- Mineral Metabolism [see Warnings and Precautions (5.2)]
- Musculoskeletal Pain [see Warnings and Precautions (5.3)]
- Osteonecrosis of the Jaw [see Warnings and Precautions (5.4)]
- Atypical Fractures Including Femoral Fractures [see Warnings and Precautions (5.5)]
- Renal Impairment [see Warnings and Precautions (5.6)]
- Patients sensitive to High Sodium Intake [see Warnings and Precautions (5.7)]

6.1 Clinical Trials Experience

Because clinical trials are conducted under widely varying conditions, adverse reaction rates observed in the clinical trials of a drug cannot be directly compared to rates in the clinical trials of another drug and may not reflect the rates observed in clinical practice.

The safety of BINOSTO (alendronate sodium) effervescent tablet 70 mg is based on clinical trial data of alendronate sodium 10 mg daily and alendronate sodium 70 mg weekly.

Treatment of Osteoporosis in Postmenopausal Women

Daily Dosing

The safety of alendronate sodium 10 mg daily in the treatment of postmenopausal osteoporosis was assessed in four clinical trials that enrolled 7453 women aged 44-84 years. Study 1 and Study 2 were identically designed, three-year, placebo-controlled, double-blind, multicenter studies (United States and Multinational n=994); Study 3 was the three year vertebral fracture cohort of the Fracture Intervention Trial [FIT] (n=2027) and Study 4 was the four-year clinical fracture cohort of FIT (n=4432). Overall, 3620 patients were exposed to placebo and 3432 patients exposed to alendronate. Patients with pre-existing gastrointestinal disease and concomitant use of non-steroidal anti-inflammatory drugs were included in these clinical trials. In Study 1 and Study 2 all women received 500 mg elemental calcium as carbonate. In Study 3 and Study 4 all women with dietary calcium intake less than 1000 mg per day received 500 mg calcium and 250 IU Vitamin D per day.

Among patients treated with alendronate 10 mg or placebo in Study 1 and Study 2, and all patients in Study 3 and Study 4, the incidence of all-cause mortality was 1.8% in the placebo group and 1.8% in the alendronate group. The incidence of serious adverse events was 30.7% in the placebo group and 30.9% in the alendronate group. The percentage of patients who discontinued the study due to any clinical adverse event was 9.5% in the placebo group and 8.9% in the alendronate group. Adverse reactions from these studies considered by the investigators as possibly, probably, or definitely drug related in greater than or equal to 1% of patients treated with either alendronate or placebo are presented in Table 1.

Table 1 Osteoporosis Treatment Studies in Postmenopausal Women Adverse Reactions Considered Possibly, Probably, or Definitely Drug Related by the Investigators and Reported in Greater Than or Equal to 1% of Patients
 | United States/Multinational Studies |  | Fracture Intervention Trial
 | Alendronate Sodium [10 mg/day for three years] | Placebo | Alendronate Sodium [5 mg/day for 2 years and 10 mg/day for either 1 or 2 additional years] | Placebo
 | % (N = 196) | % (N = 397) | % (N = 3236) | % (N = 3223)
Gastrointestinal
Abdominal pain | 6.6 | 4.8 | 1.5 | 1.5
Nausea | 3.6 | 4.0 | 1.1 | 1.5
Dyspepsia | 3.6 | 3.5 | 1.1 | 1.2
Constipation | 3.1 | 1.8 | 0.0 | 0.2
Diarrhea | 3.1 | 1.8 | 0.6 | 0.3
Flatulence | 2.6 | 0.5 | 0.2 | 0.3
Acid regurgitation | 2.0 | 4.3 | 1.1 | 0.9
Esophageal ulcer | 1.5 | 0.0 | 0.1 | 0.1
Vomiting | 1.0 | 1.5 | 0.2 | 0.3
Dysphagia | 1.0 | 0.0 | 0.1 | 0.1
Abdominal distention | 1.0 | 0.8 | 0.0 | 0.0
Gastritis | 0.5 | 1.3 | 0.6 | 0.7
Musculoskeletal
Musculoskeletal (bone, muscle or joint) pain | 4.1 | 2.5 | 0.4 | 0.3
Muscle cramp | 0.0 | 1.0 | 0.2 | 0.1
Nervous system/psychiatric
Headache | 2.6 | 1.5 | 0.2 | 0.2
Dizziness | 0.0 | 1.0 | 0.0 | 0.1
Special senses
Taste perversion | 0.5 | 1.0 | 0.1 | 0.0

Rarely, rash and erythema have occurred.

Gastrointestinal Adverse Reactions: One patient treated with alendronate sodium (10 mg/day), who had a history of peptic ulcer disease and gastrectomy and who was taking concomitant aspirin developed an anastomotic ulcer with mild hemorrhage, which was considered drug related. Aspirin and alendronate sodium were discontinued and the patient recovered. In the Study 1 and Study 2 populations, 49-54% had a history of gastrointestinal disorders at baseline and 54-89% used nonsteroidal anti-inflammatory drugs or aspirin at some time during the studies [see Warnings and Precautions (5.1)].

Laboratory Test Findings: In double-blind, multicenter, controlled studies, asymptomatic, mild, and transient decreases in serum calcium and phosphate were observed in approximately 18% and 10%, respectively, of patients taking alendronate versus approximately 12% and 3% of those taking placebo. However, the incidences of decreases in serum calcium to less than 8.0 mg/dL (2.0 mM) and serum phosphate to less than or equal to 2.0 mg/dL (0.65 mM) were similar in both treatment groups.

Weekly Dosing

The safety of alendronate sodium 70 mg once weekly for the treatment of postmenopausal osteoporosis was assessed in a one-year, double-blind, multicenter study comparing alendronate 70 mg once weekly and alendronate 10 mg daily. The overall safety and tolerability profiles of once weekly alendronate 70 mg and alendronate 10 mg daily were similar. The adverse reactions considered by the investigators as possibly, probably, or definitely drug related in greater than or equal to 1% of patients in either treatment group are presented in Table 2.

Table 2 Osteoporosis Treatment Studies in Postmenopausal Women Adverse Reactions Considered Possibly, Probably, or Definitely Drug Related by the Investigators and Reported in Greater Than or Equal to 1% of Patients
 | Once Weekly Alendronate Sodium 70 mg % (N = 519) | Once Daily Alendronate Sodium 10 mg % (N = 370)
Gastrointestinal
Abdominal pain | 3.7 | 3.0
Dyspepsia | 2.7 | 2.2
Acid regurgitation | 1.9 | 2.4
Nausea | 1.9 | 2.4
Abdominal distention | 1.0 | 1.4
Constipation | 0.8 | 1.6
Flatulence | 0.4 | 1.6
Gastritis | 0.2 | 1.1
Gastric ulcer | 0.0 | 1.1
Musculoskeletal
Musculoskeletal (bone, muscle, joint) pain | 2.9 | 3.2
Muscle cramp | 0.2 | 1.1

Osteoporosis in Men

In two placebo-controlled, double-blind, multicenter studies in men (a two-year study of alendronate sodium 10 mg/day and a one-year study of once weekly alendronate sodium 70 mg) the rates of discontinuation of therapy due to any clinical adverse event were 2.7% for alendronate 10 mg/day vs. 10.5% for placebo, and 6.4% for once weekly alendronate 70 mg vs. 8.6% for placebo. The adverse reactions considered by the investigators as possibly, probably, or definitely drug related in greater than or equal to 2% of patients treated with either alendronate or placebo are presented in the following table.

Table 3 Osteoporosis Studies in Men Adverse Reactions Considered Possibly, Probably, or Definitely Drug Related by the Investigators and Reported in Greater Than or Equal to 2% of Patients
 | Two-Year Study |  | One-Year Study
 | Once Daily Alendronate Sodium |  | Once Weekly Alendronate Sodium
 | 10 mg % (N = 146) | Placebo % (N = 95) | 70 mg % (N = 109) | Placebo % (N = 58)
Gastrointestinal
Acid regurgitation | 4.1 | 3.2 | 0.0 | 0.0
Flatulence | 4.1 | 1.1 | 0.0 | 0.0
Gastroesophageal reflux disease | 0.7 | 3.2 | 2.8 | 0.0
Dyspepsia | 3.4 | 0.0 | 2.8 | 1.7
Diarrhea | 1.4 | 1.1 | 2.8 | 0.0
Abdominal pain | 2.1 | 1.1 | 0.9 | 3.4
Nausea | 2.1 | 0.0 | 0.0 | 0.0

6.2 Post-Marketing Experience

The following adverse reactions have been identified during post-approval use of alendronate sodium or bisphosphonate products. Because these reactions are reported voluntarily from a population of uncertain size, it is not always possible to reliably estimate their frequency or establish a causal relationship to drug exposure.

Body as a Whole: hypersensitivity reactions including urticaria and angioedema. Transient symptoms of myalgia, malaise, asthenia and fever have been reported with alendronate, typically in association with initiation of treatment. Symptomatic hypocalcemia has occurred, generally in association with predisposing conditions. Peripheral edema.

Gastrointestinal: esophagitis, esophageal erosions, esophageal ulcers, esophageal stricture or perforation, and oropharyngeal ulceration. Gastric or duodenal ulcers, some severe and with complications have also been reported [see Dosage and Administration (2.3); Warnings and Precautions (5.1)].

Dental: Localized osteonecrosis of the jaw, generally associated with tooth extraction and/or local infection with delayed healing, has been reported [see Warnings and Precautions (5.4)].

Musculoskeletal: bone, joint, and/or muscle pain, occasionally severe and incapacitating [see Warnings and Precautions (5.3)]; joint swelling; low-energy femoral shaft and subtrochanteric fractures, and atypical fractures of other bones [see Warnings and Precautions (5.5].

Nervous system: dizziness and vertigo.

Pulmonary: acute asthma exacerbations

Skin: rash (occasionally with photosensitivity), pruritus, alopecia, severe skin reactions, including Stevens-Johnson syndrome and toxic epidermal necrolysis.

Special Senses: uveitis, scleritis or episcleritis. Cholesteatoma of the external auditory canal (focal osteonecrosis).

7 DRUG INTERACTIONS

7.1 Calcium Supplements/Antacids

Co-administration of BINOSTO and calcium, antacids, or oral medications containing multivalent cations will interfere with absorption of BINOSTO. Therefore, instruct patients to wait at least one-half hour after taking BINOSTO before taking any other oral medications.

7.2 Aspirin

In clinical studies, the incidence of upper gastrointestinal adverse events was increased in patients receiving concomitant therapy with daily doses of alendronate sodium greater than 10 mg and aspirin-containing products.

7.3 Nonsteroidal Anti-inflammatory Drugs (NSAIDs)

BINOSTO may be administered to patients taking NSAIDs. In a 3-year, controlled, clinical study (n=2027) during which a majority of patients received concomitant NSAIDs, the incidence of upper gastrointestinal adverse events was similar in patients taking alendronate sodium 5 or 10 mg/day compared to those taking placebo. However, since NSAID use is associated with gastrointestinal irritation, caution should be used during concomitant use with BINOSTO.

7.4 Levothyroxine

The bioavailability of alendronate was slightly decreased when BINOSTO and levothyroxine were co-administered to healthy subjects [see Clinical Pharmacology (12.3)].

8 USE IN SPECIFIC POPULATIONS

8.1 Pregnancy

Risk Summary

Available data on the use of BINOSTO in pregnant women are insufficient to inform a drug-associated risk of adverse maternal or fetal outcomes. Discontinue BINOSTO when pregnancy is recognized.

In animal reproduction studies, daily oral administration of alendronate to rats from before mating through the end of gestation or lactation showed decreased postimplantation survival and decreased pup body weight gain starting at doses equivalent to less than half of the highest recommended 40 mg clinical daily dose (based on body surface area, mg/m^2). Oral administration of alendronate to rats during organogenesis resulted in reduced fetal ossification starting at doses 3 times the 40 mg clinical daily dose. No similar fetal effects were observed in pregnant rabbits dosed orally during organogenesis at doses equivalent to approximately 10 times the 40 mg clinical daily dose.

Delayed or failed delivery of offspring, protracted parturition, and late pregnancy maternal and fetal deaths due to maternal hypocalcemia occurred in rats at oral doses as low as one tenth the 40 mg clinical daily dose (See Data).

Bisphosphonates are incorporated into the bone matrix, from which they are gradually released over a period of years. The amount of bisphosphonate incorporated into adult bone and available for release into the systemic circulation is directly related to the dose and duration of bisphosphonate use. Consequently, based on the mechanism of action of bisphosphonates, there is a potential risk of fetal harm, predominantly skeletal, if a woman becomes pregnant after completing a course of bisphosphonate therapy. The impact of variables such as time between cessation of bisphosphonate therapy to conception, the particular bisphosphonate used, and the route of administration (intravenous versus oral) on the risk has not been studied.

The estimated background risk of major birth defects and miscarriage for the indicated population(s) is unknown. All pregnancies have a background risk of birth defects, loss, or other adverse outcomes. In the U.S. general population, the estimated background risks of major birth defects and miscarriage in clinically recognized pregnancies is 2-4% and 15-20%, respectively.

Data

Animal Data

Reproduction studies in rats dosed orally from before mating to the end of gestation or lactation showed decreased postimplantation survival starting at 2 mg/kg/day and decreased body weight gain starting at 1 mg/kg/day, doses equivalent to less than half the 40 mg clinical daily dose based on body surface area, mg/m^2. Incidence of incomplete fetal ossification in vertebral, skull, and sternebral bones were increased in rats dosed orally during organogenesis starting at 10 mg/kg/day (approximately 3 times the 40 mg clinical daily dose). No similar fetal effects were observed in pregnant rabbits dosed orally during organogenesis at up to 35 mg/kg/day (equivalent to approximately 10 times the 40 mg clinical daily dose).

Both total and ionized calcium decreased in pregnant rats dosed orally with 15 mg/kg/day alendronate (approximately 4 times the 40 mg clinical daily dose) resulting in delays and failures of delivery. Protracted parturition due to maternal hypocalcemia was observed when rats were treated from before mating through gestation starting at 0.5 mg/kg/day (approximately one tenth the 40 mg clinical daily dose). Maternotoxicity (late pregnancy deaths) also occurred in female rats treated orally with 15 mg/kg/day (approximately 4 times the 40 mg clinical daily dose) for varying gestational time periods. These maternal deaths were lessened but not eliminated by cessation of treatment. Calcium supplementation in the drinking water or by subcutaneous minipump to rats dosed orally with 15 mg/kg/day alendronate could not ameliorate the hypocalcemia or prevent the dystocia-related maternal and neonatal deaths. However, intravenous calcium supplementation prevented maternal, but not neonatal deaths.

8.2 Lactation

Risk Summary

It is not known whether alendronate is present in human breast milk, affects human milk production, or has effects on the breastfed infant. The developmental and health benefits of breastfeeding should be considered along with the mother's clinical need for BINOSTO and any potential adverse effects on the breastfed child from BINOSTO or from the underlying maternal condition.

8.4 Pediatric Use

BINOSTO is not indicated for use in pediatric patients.

The safety and efficacy of alendronate sodium were examined in a randomized, double-blind, placebo-controlled two-year study of 139 pediatric patients, aged 4-18 years, with severe osteogenesis imperfecta (OI). One-hundred-and-nine patients were randomized to 5 mg alendronate sodium daily (weight less than 40 kg) or 10 mg alendronate sodium daily (weight greater than or equal to 40 kg) and 30 patients to placebo. The mean baseline lumbar spine BMD Z-score of the patients was -4.5. The mean change in lumbar spine BMD Z-score from baseline to Month 24 was 1.3 in the alendronate-treated patients and 0.1 in the placebo- treated patients. Treatment with alendronate sodium did not reduce the risk of fracture. Sixteen percent of the alendronate-treated patients who sustained a radiologically-confirmed fracture by Month 12 of the study had delayed fracture healing (callus remodeling) or fracture non-union when assessed radiographically at Month 24 compared with 9% of the placebo-treated patients. In alendronate-treated patients, bone histomorphometry data obtained at Month 24 demonstrated decreased bone turnover and delayed mineralization time; however, there were no mineralization defects. There were no statistically significant differences between the alendronate sodium and placebo groups in reduction of bone pain. The oral bioavailability in children was similar to that observed in adults.

The overall safety profile of alendronate sodium in osteogenesis imperfecta patients treated for up to 24 months was generally similar to that of adults with osteoporosis treated with alendronate sodium. However, there was an increased occurrence of vomiting in osteogenesis imperfecta patients treated with alendronate sodium compared to placebo. During the 24-month treatment period, vomiting was observed in 32 of 109 (29.4%) patients treated with alendronate sodium and 3 of 30 (10%) patients treated with placebo.

In a pharmacokinetic study, 6 of 24 pediatric osteogenesis imperfecta patients who received a single oral dose of alendronate sodium 35 or 70 mg developed fever, flu-like symptoms, and/or mild lymphocytopenia within 24 to 48 hours after administration. These events, lasting no more than 2 to 3 days and responding to acetaminophen, are consistent with an acute-phase response that has been reported in patients receiving bisphosphonates, including alendronate sodium. [See Adverse Reactions (6.2).]

8.5 Geriatric Use

Of the patients receiving alendronate sodium in the Fracture Intervention Trial (FIT), 71% (n=2302) were greater than or equal to 65 years of age and 17% (n=550) were greater than or equal to 75 years of age. Of the patients receiving alendronate sodium in the United States and Multinational osteoporosis treatment studies in women and osteoporosis studies in men, [see Clinical Studies (14.1), (14.2)], 45% and 54%, respectively, were 65 years of age or over. No overall differences in efficacy or safety were observed between these patients and younger patients, but greater sensitivity of some older individuals cannot be ruled out.

8.6 Renal Impairment

BINOSTO is not recommended for patients with creatinine clearance less than 35 mL/min. No dosage adjustment is necessary in patients with creatinine clearance values between 35-60 mL/min [see Clinical Pharmacology (12.3)].

8.7 Hepatic Impairment

As there is evidence that alendronate is not metabolized or excreted in the bile, no studies were conducted in patients with hepatic impairment. No dosage adjustment is necessary [see Clinical Pharmacology (12.3)].

10 OVERDOSAGE

Significant lethality after single oral doses was seen in female rats and mice at 552 mg/kg (3256 mg/m^2) and 966 mg/kg (2898 mg/m^2), respectively. In males, these values were slightly higher, 626 and 1280 mg/kg, respectively. There was no lethality in dogs at oral doses up to 200 mg/kg (4000 mg/m^2).

No specific information is available on the treatment of overdosage with BINOSTO. Hypocalcemia, hypophosphatemia, and upper gastrointestinal adverse events, such as upset stomach, heartburn, esophagitis, gastritis, or ulcer, may result from oral overdosage. Milk or antacids should be given to bind alendronate. Due to the risk of esophageal irritation, vomiting should not be induced and the patient should remain fully upright.

Dialysis would not be beneficial.

11 DESCRIPTION

BINOSTO (alendronate sodium) is a bisphosphonate that acts as a specific inhibitor of osteoclast-mediated bone resorption. Bisphosphonates are synthetic analogs of pyrophosphate that bind to the hydroxyapatite found in bone.

Alendronate sodium is chemically described as (4 amino-1-hydroxybutylidene) bisphosphonic acid, monosodium salt, trihydrate. The molecular formula of alendronate sodium is C4H12NNaO7P2 ∙ 3H2O and its molecular weight is 325.12. The structural formula of alendronate sodium is

Alendronate sodium is a white or almost white crystalline powder that is soluble in water, very slightly soluble in methanol, and practically insoluble in methylene chloride.

BINOSTO for oral administration is an effervescent tablet formulation that must be dissolved in water before use. Each individual tablet contains 91.37 mg of alendronate sodium, which is equivalent to 70 mg of free alendronic acid. Each tablet also contains the following inactive ingredients: monosodium citrate anhydrous, citric acid anhydrous, sodium hydrogen carbonate, and sodium carbonate anhydrous as buffering agents, strawberry flavor, acesulfame potassium, and sucralose.

70 mg of BINOSTO effervescent tablet contains 603 mg of sodium and 17 mg of phosphorus.

Once the effervescent tablet is dissolved in water, the alendronate sodium is present in a citrate-buffered solution of pH 4.8 to 5.4.

12 CLINICAL PHARMACOLOGY

12.1 Mechanism of Action

Animal studies have indicated the following mode of action. At the cellular level, alendronate shows preferential localization to sites of bone resorption, specifically under osteoclasts. The osteoclasts adhere normally to the bone surface but lack the ruffled border that is indicative of active resorption. Alendronate does not interfere with osteoclast recruitment or attachment, but it does inhibit osteoclast activity. Studies in mice on the localization of radioactive [^3H]alendronate in bone showed about 10-fold higher uptake on osteoclast surfaces than on osteoblast surfaces. Bones examined 6 and 49 days after [^3H]alendronate administration in rats and mice, respectively, showed that normal bone was formed on top of the alendronate, which was incorporated inside the matrix. While incorporated in bone matrix, alendronate is not pharmacologically active. Thus, alendronate must be continuously administered to suppress osteoclasts on newly formed resorption surfaces. Histomorphometry in baboons and rats showed that alendronate treatment reduces bone turnover (i.e., the number of sites at which bone is remodeled). In addition, bone formation exceeds bone resorption at these remodeling sites, leading to progressive gains in bone mass.

12.2 Pharmacodynamics

Alendronate is a bisphosphonate that binds to bone hydroxyapatite and specifically inhibits the activity of osteoclasts, the bone-resorbing cells. Alendronate reduces bone resorption with no direct effect on bone formation, although the latter process is ultimately reduced because bone resorption and formation are coupled during bone turnover.

Osteoporosis in Postmenopausal Women

Osteoporosis is characterized by low bone mass that leads to an increased risk of fracture. The diagnosis can be confirmed by the finding of low bone mass, evidence of fracture on x-ray, a history of osteoporotic fracture, or height loss or kyphosis, indicative of vertebral (spinal) fracture. Osteoporosis occurs in both males and females but is most common among women following the menopause, when bone turnover increases and the rate of bone resorption exceeds that of bone formation. These changes result in progressive bone loss and lead to osteoporosis in a significant proportion of women over age 50. Fractures, usually of the spine, hip, and wrist, are the common consequences. From age 50 to age 90, the risk of hip fracture in white women increases 50-fold and the risk of vertebral fracture 15- to 30-fold. It is estimated that approximately 40% of 50-year-old women will sustain one or more osteoporosis-related fractures of the spine, hip, or wrist during their remaining lifetimes. Hip fractures, in particular, are associated with substantial morbidity, disability, and mortality.

Daily oral doses of alendronate sodium (5, 20, and 40 mg for six weeks) in postmenopausal women produced biochemical changes indicative of dose-dependent inhibition of bone resorption, including decreases in urinary calcium and urinary markers of bone collagen degradation (such as deoxypyridinoline and cross-linked N-telopeptides of type I collagen). These biochemical changes tended to return toward baseline values as early as 3 weeks following the discontinuation of therapy with alendronate and did not differ from placebo after 7 months.

Long-term treatment of osteoporosis with alendronate sodium 10 mg/day (for up to five years) reduced urinary excretion of markers of bone resorption, deoxypyridinoline and cross-linked N-telopeptides of type l collagen, by approximately 50% and 70%, respectively, to reach levels similar to those seen in healthy premenopausal women. Similar decreases were seen in patients in osteoporosis prevention studies who received alendronate sodium 5 mg/day. The decrease in the rate of bone resorption indicated by these markers was evident as early as 1 month and at 3 to 6 months reached a plateau that was maintained for the entire duration of treatment with alendronate sodium. In osteoporosis treatment studies alendronate sodium 10 mg/day decreased the markers of bone formation, osteocalcin and bone specific alkaline phosphatase by approximately 50%, and total serum alkaline phosphatase by approximately 25 to 30% to reach a plateau after 6 to 12 months. In osteoporosis prevention studies alendronate sodium 5 mg/day decreased osteocalcin and total serum alkaline phosphatase by approximately 40% and 15%, respectively. Similar reductions in the rate of bone turnover were observed in postmenopausal women during one-year studies with once weekly alendronate sodium 70 mg for the treatment of osteoporosis and once weekly alendronate sodium 35 mg for the prevention of osteoporosis. These data indicate that the rate of bone turnover reached a new steady state, despite the progressive increase in the total amount of alendronate deposited within bone.

As a result of inhibition of bone resorption, asymptomatic reductions in serum calcium and phosphate concentrations were also observed following treatment with alendronate sodium. In the long-term studies, reductions from baseline in serum calcium (approximately 2%) and phosphate (approximately 4 to 6%) were evident the first month after the initiation of alendronate sodium 10 mg. No further decreases in serum calcium were observed for the five-year duration of treatment; however, serum phosphate returned toward prestudy levels during years three through five. Similar reductions were observed with alendronate sodium 5 mg/day. In one-year studies with once weekly alendronate sodium 35 and 70 mg, similar reductions were observed at 6 and 12 months. The reduction in serum phosphate may reflect not only the positive bone mineral balance due to alendronate sodium but also a decrease in renal phosphate reabsorption.

Osteoporosis in Men

Treatment of men with osteoporosis with alendronate sodium 10 mg/day for two years reduced urinary excretion of cross-linked N-telopeptides of type I collagen by approximately 60% and bone-specific alkaline phosphatase by approximately 40%. Similar reductions were observed in a one-year study in men with osteoporosis receiving once weekly alendronate sodium 70 mg.

12.3 Pharmacokinetics

Absorption

Relative to an intravenous (IV) reference dose, the mean oral bioavailability of alendronate in women was 0.64% for doses ranging from 5 to 70 mg when administered after an overnight fast and two hours before a standardized breakfast. Oral bioavailability of the 10 mg tablet in men (0.59%) was similar to that in women when administered after an overnight fast and 2 hours before breakfast.

BINOSTO 70 mg effervescent tablet and alendronate sodium 70 mg tablet are bioequivalent.

A study evaluating the effect of food on the bioavailability of BINOSTO was performed in 119 healthy women. Bioavailability was decreased (by approximately 50%) when 70 mg alendronate sodium was administered 15 minutes before a standardized breakfast, when compared to dosing 4 hours before eating.

In studies of treatment and prevention of osteoporosis, alendronate was effective when administered at least 30 minutes before breakfast.

Bioavailability was negligible whether alendronate sodium was administered with or up to 2 hours after a standardized breakfast. Concomitant administration of alendronate with coffee or orange juice reduced bioavailability by approximately 60%.

Distribution

Preclinical studies (in male rats) show that alendronate sodium transiently distributes to soft tissues following 1 mg/kg IV administration but is then rapidly redistributed to bone or excreted in the urine. The mean steady-state volume of distribution, exclusive of bone, is at least 28 L in humans. Concentrations of drug in plasma following therapeutic oral doses are too low (less than 5 ng/mL) for analytical detection. Protein binding in human plasma is approximately 78%.

Metabolism

There is no evidence that alendronate sodium is metabolized in animals or humans.

Excretion

Following a single IV dose of [^14C]alendronate, approximately 50% of the radioactivity was excreted in the urine within 72 hours and little or no radioactivity was recovered in the feces. Following a single 10 mg IV dose, the renal clearance of alendronate was 71 mL/min (64, 78; 90% confidence interval [CI]), and systemic clearance did not exceed 200 mL/min. Plasma concentrations fell by more than 95% within 6 hours following IV administration. The terminal half-life in humans is estimated to exceed 10 years, probably reflecting release of alendronate from the skeleton. Based on the above, it is estimated that after 10 years of oral treatment with alendronate sodium (10 mg daily) the amount of alendronate released daily from the skeleton is approximately 25% of that absorbed from the gastrointestinal tract.

Specific Populations

Gender: Bioavailability and the fraction of an intravenous dose excreted in urine were similar in men and women.

Geriatric: Bioavailability and disposition (urinary excretion) were similar in elderly and younger patients. No dosage adjustment is necessary in elderly patients.

Race: Pharmacokinetic differences due to race have not been studied.

Renal Impairment: Preclinical studies show that, in rats with kidney failure, increasing amounts of drug are present in plasma, kidney, spleen, and tibia. In healthy controls, drug that is not deposited in bone is rapidly excreted in the urine. No evidence of saturation of bone uptake was found after 3 weeks dosing with cumulative intravenous doses of 35 mg/kg in young male rats. Although no formal renal impairment pharmacokinetic study has been conducted in patients, it is likely that, as in animals, elimination of alendronate via the kidney will be reduced in patients with impaired renal function. Therefore, somewhat greater accumulation of alendronate in bone might be expected in patients with impaired renal function.

No dosage adjustment is necessary for patients with creatinine clearance 35 to 60 mL/min. BINOSTO is not recommended for patients with creatinine clearance less than 35 mL/min due to lack of experience with alendronate in renal failure.

Hepatic Impairment: As there is evidence that alendronate is not metabolized or excreted in the bile, no studies were conducted in patients with hepatic impairment. No dosage adjustment is necessary.

Drug Interactions

Ranitidine: Intravenous ranitidine was shown to double the bioavailability of oral alendronate. The clinical significance of this increased bioavailability and whether similar increases will occur in patients given oral H2-antagonists is unknown.

Prednisone: In healthy subjects, oral prednisone (20 mg three times daily for five days) did not produce a clinically meaningful change in the oral bioavailability of alendronate (a mean increase ranging from 20 to 44%).

Calcium and Multivalent Cations: Products containing calcium and other multivalent cations are likely to interfere with absorption of alendronate.

Levothyroxine: The geometric mean AUC(0-∞) and Cmax of alendronate decreased by 7% (point estimate: 0.93; 90% CI: 0.79-1.08) and 9% (point estimate: 0.91; 90% CI: 0.77-1.08), respectively, when a single dose of BINOSTO (70 mg alendronate) and 600 mcg levothyroxine were given concomitantly to 29 healthy male and female subjects.

13 NONCLINICAL TOXICOLOGY

13.1 Carcinogenesis, Mutagenesis, Impairment of Fertility

Harderian gland (a retro-orbital gland not present in humans) adenomas were increased in high-dose female mice (p=0.003) in a 92-week oral carcinogenicity study at doses of alendronate of 1, 3, and 10 mg/kg/day (males) or 1, 2, and 5 mg/kg/day (females). These doses are equivalent to 0.12 to 1.2 times a maximum recommended daily dose of 40 mg, based on surface area, mg/m^2. The relevance of this finding to humans is unknown.

Parafollicular cell (thyroid) adenomas were increased in high-dose male rats (p=0.003) in a 2-year oral carcinogenicity study at doses of 1 and 3.75 mg/kg body weight. These doses are equivalent to 0.26 and 1 times a 40 mg human daily dose based on surface area, mg/m^2. The relevance of this finding to humans is unknown.

Alendronate sodium was not genotoxic in the in vitro microbial mutagenesis assay with and without metabolic activation, in an in vitro mammalian cell mutagenesis assay, in an in vitro alkaline elution assay in rat hepatocytes, and in an in vivo chromosomal aberration assay in mice. In an in vitro chromosomal aberration assay in Chinese hamster ovary cells, however, alendronate gave equivocal results.

Alendronate sodium had no effect on fertility (male or female) in rats at oral doses up to 5 mg/kg/day (1.3 times a 40 mg human daily dose based on surface area, mg/m^2).

13.2 Animal Toxicology and/or Pharmacology

The relative inhibitory activities on bone resorption and mineralization of alendronate and etidronate were compared in the Schenk assay, which is based on histological examination of the epiphyses of growing rats. In this assay, the lowest dose of alendronate that interfered with bone mineralization (leading to osteomalacia) was 6000-fold the antiresorptive dose. The corresponding ratio for etidronate was one to one. These data suggest that alendronate administered in therapeutic doses is highly unlikely to induce osteomalacia.

14 CLINICAL STUDIES

14.1 Treatment of Osteoporosis in Postmenopausal Women

BINOSTO (alendronate sodium) effervescent tablet 70 mg is bioequivalent to alendronate sodium tablet 70 mg. The fracture reduction efficacy and bone mineral density changes attributed to BINOSTO are based on clinical trial data of alendronate sodium 10 mg daily and alendronate sodium 70 mg weekly.

Daily Dosing

The efficacy of alendronate sodium 10 mg daily was assessed in four clinical trials. Study 1, a three-year, multicenter double-blind, placebo-controlled, US clinical study enrolled 478 patients with a BMD T-score at or below minus 2.5 with or without a prior vertebral fracture; Study 2, a three-year, multicenter double blind placebo controlled Multinational clinical study enrolled 516 patients with a BMD T-score at or below minus 2.5 with or without a prior vertebral fracture; Study 3, the Three-Year Study of the Fracture Intervention Trial (FIT) a study which enrolled 2027 postmenopausal patients with at least one baseline vertebral fracture; and Study 4, the Four-Year Study of FIT: a study which enrolled 4432 postmenopausal patients with low bone mass but without a baseline vertebral fracture.

Effect on Fracture Incidence

To assess the effects of alendronate sodium on the incidence of vertebral fractures (detected by digitized radiography; approximately one third of these were clinically symptomatic), the U.S. and Multinational studies were combined in an analysis that compared placebo to the pooled dosage groups of alendronate sodium (5 or 10 mg for three years or 20 mg for two years followed by 5 mg for one year). There was a statistically significant reduction in the proportion of patients treated with alendronate experiencing one or more new vertebral fractures relative to those treated with placebo (3.2% vs. 6.2%; a 48% relative risk reduction). A reduction in the total number of new vertebral fractures (4.2 vs. 11.3 per 100 patients) was also observed. In the pooled analysis, patients who received alendronate had a loss in stature that was statistically significantly less than was observed in those who received placebo (-3.0 mm vs. -4.6 mm). The Fracture Intervention Trial (FIT) consisted of two studies in postmenopausal women: the Three-Year Study of patients who had at least one baseline radiographic vertebral fracture and the Four-Year Study of patients with low bone mass but without a baseline vertebral fracture. In both studies of FIT, 96% of randomized patients completed the studies (i.e., had a closeout visit at the scheduled end of the study); approximately 80% of patients were still taking study medication upon completion.

Fracture Intervention Trial: Three-Year Study (patients with at least one baseline radiographic vertebral fracture)

This randomized, double-blind, placebo-controlled, 2027-patient study (alendronate, n=1022; placebo, n=1005) demonstrated that treatment with alendronate sodium resulted in statistically significant reductions in fracture incidence at three years as shown in Table 4.

Table 4 Effect of Alendronate Sodium on Fracture Incidence in the Three-Year Study of FIT (Patients With Vertebral Fracture at Baseline)
 | Percent of Patients
 | Alendronate Sodium (N = 1022) | Placebo (N = 1005) | Absolute Reduction in Fracture Incidence | Relative Reduction in Fracture Risk %
Patients with:
Vertebral fractures (diagnosed by X-ray) [Number evaluable for vertebral fractures: alendronate, n=984; placebo, n=966]
≥1 new vertebral fracture | 7.9 | 15.0 | 7.1 | 47 [p<0.001,]
≥2 new vertebral fractures | 0.5 | 4.9 | 4.4 | 90
Clinical (symptomatic) fractures
Any clinical (symptomatic) fracture | 13.8 | 18.1 | 4.3 | 26 [p=0.007,]
≥1 clinical (symptomatic) vertebral fracture | 2.3 | 5.0 | 2.7 | 54 [p<0.01,]
Hip fracture | 1.1 | 2.2 | 1.1 | 51 [p<0.05]
Wrist (forearm) fracture | 2.2 | 4.1 | 1.9 | 48

Furthermore, in this population of patients with baseline vertebral fracture, treatment with alendronate sodium significantly reduced the incidence of hospitalizations (25.0% vs. 30.7%).

In the Three-Year Study of FIT, fractures of the hip occurred in 22 (2.2%) of 1005 patients on placebo and 11 (1.1%) of 1022 patients on alendronate sodium, p=0.047. Figure 1 displays the cumulative incidence of hip fractures in this study.

Figure 1 Cumulative Incidence of Hip Fractures in the Three-Year Study of FIT
(Patients With Radiographic Vertebral Fracture at Baseline)

Fracture Intervention Trial: Four-Year Study (patients with low bone mass but without a baseline radiographic vertebral fracture)

This randomized, double-blind, placebo-controlled, 4432-patient study (alendronate, n=2214; placebo, n=2218) further investigated the reduction in fracture incidence due to alendronate sodium. The intent of the study was to recruit women with osteoporosis, defined as a baseline femoral neck BMD at least two standard deviations below the mean for young adult women. However, due to subsequent revisions to the normative values for femoral neck BMD, 31% of patients were found not to meet this entry criterion and thus this study included both osteoporotic and non-osteoporotic women. The results are shown in Table 5 for the patients with osteoporosis.

Table 5 Effect of Alendronate on Fracture Incidence in Osteoporotic [Baseline femoral neck BMD at least 2 SD below the mean for young adult women] Patients in the Four-Year Study of FIT (Patients Without Vertebral Fracture at Baseline)
 | Percent of Patients
 | Alendronate Sodium (N = 1545) | Placebo (N = 1521) | Absolute Reduction in Fracture Incidence | Relative Reduction in Fracture Risk %
Patients with:
Vertebral fractures (diagnosed by X-ray) [Number evaluable for vertebral fractures: alendronate, n=1426; placebo, n=1428]
≥1 new vertebral fracture | 2.5 | 4.8 | 2.3 | 48 [p<0.001,]
≥2 new vertebral fractures | 0.1 | 0.6 | 0.5 | 78 [p=0.035,]
Clinical (symptomatic) fractures
Any clinical (symptomatic) fracture | 12.9 | 16.2 | 3.3 | 22 [p=0.01]
≥1 clinical (symptomatic) vertebral fracture | 1.0 | 1.6 | 0.6 | 41(NS) [Not significant. This study was not powered to detect differences at these sites.]
Hip fracture | 1.0 | 1.4 | 0.4 | 29(NS)
Wrist (forearm) fracture | 3.9 | 3.8 | -0.1 | NS

Fracture Results Across Studies

In the Three-Year Study of FIT, alendronate sodium reduced the percentage of women experiencing at least one new radiographic vertebral fracture from 15.0% to 7.9% (47% relative risk reduction, p<0.001); in the Four-Year Study of FIT, the percentage was reduced from 3.8% to 2.1% (44% relative risk reduction, p=0.001); and in the combined U.S./Multinational studies, from 6.2% to 3.2% (48% relative risk reduction, p=0.034).

Alendronate sodium reduced the percentage of women experiencing multiple (two or more) new vertebral fractures from 4.2% to 0.6% (87% relative risk reduction, p<0.001) in the combined U.S./Multinational studies and from 4.9% to 0.5% (90% relative risk reduction, p<0.001) in the Three-Year Study of FIT. In the Four-Year Study of FIT, alendronate sodium reduced the percentage of osteoporotic women experiencing multiple vertebral fractures from 0.6% to 0.1% (78% relative risk reduction, p=0.035).

Thus, alendronate sodium reduced the incidence of radiographic vertebral fractures in osteoporotic women whether or not they had a previous radiographic vertebral fracture.

Effect on Bone Mineral Density

The bone mineral density efficacy of alendronate sodium 10 mg once daily in postmenopausal women, 44 to 84 years of age, with osteoporosis (lumbar spine bone mineral density [BMD] of at least 2 standard deviations below the premenopausal mean) was demonstrated in 4 double-blind, placebo-controlled clinical studies of 2 or 3 years' duration.

Figure 2 shows the mean increases in BMD of the lumbar spine, femoral neck, and trochanter in patients receiving alendronate sodium 10 mg/day relative to placebo-treated patients at three years for each of these studies.

Figure 2 Osteoporosis Treatment Studies in Postmenopausal Women Increase in BMD Alendronate Sodium 10 mg/day at Three Years

At 3 years significant increases in BMD, relative both to baseline and placebo, were seen at each measurement site in each study in patients who received alendronate 10 mg/day. Total body BMD also increased significantly in each study, suggesting that the increases in bone mass of the spine and hip did not occur at the expense of other skeletal sites. Increases in BMD were evident as early as 3 months and continued throughout the 3 years of treatment. (See figures below for lumbar spine results.) In the 2-year extension of these studies, treatment of 147 patients with alendronate sodium 10 mg/day resulted in continued increases in BMD at the lumbar spine and trochanter (absolute additional increases between years 3 and 5: lumbar spine, 0.94%; trochanter, 0.88%). BMD at the femoral neck, forearm and total body were maintained. Alendronate sodium was similarly effective regardless of age, race, baseline rate of bone turnover, and baseline BMD in the range studied (at least 2 standard deviations below the premenopausal mean).

Figure 3 Osteoporosis Treatment in Studies in Postmenopausal Women
Time Course Effect of Alendronate Sodium 10 mg/day Versus Placebo: Lumbar Spine BMD Percent Change From Baseline

In patients with postmenopausal osteoporosis treated with alendronate sodium 10 mg/day for one or two years, the effects of treatment withdrawal were assessed. Following discontinuation, there were no further increases in bone mass and the rates of bone loss were similar to those of the placebo groups.

Bone Histology

Bone histology in 270 postmenopausal patients with osteoporosis treated with alendronate sodium at doses ranging from 1 to 20 mg/day for one, two, or three years revealed normal mineralization and structure, as well as the expected decrease in bone turnover relative to placebo. These data, together with the normal bone histology and increased bone strength observed in rats and baboons exposed to long-term alendronate treatment, support the conclusion that bone formed during therapy with alendronate sodium is of normal quality.

Effect on height

Alendronate sodium, over a three- or four-year period, was associated with statistically significant reductions in loss of height vs. placebo in patients with and without baseline radiographic vertebral fractures. At the end of the FIT studies the between-treatment group differences were 3.2 mm in the Three-Year Study and 1.3 mm in the Four-Year Study.

Weekly dosing

The therapeutic equivalence of once weekly alendronate sodium 70 mg (n=519) and alendronate sodium 10 mg daily (n=370) was demonstrated in a one-year, double-blind, multicenter study of postmenopausal women with osteoporosis. In the primary analysis of completers, the mean increases from baseline in lumbar spine BMD at 1 year were 5.1% (4.8, 5.4%; 95% CI) in the 70 mg once-weekly group (n=440) and 5.4% (5.0, 5.8%; 95% CI) in the 10 mg daily group (n=330). The 2 treatment groups were also similar with regard to BMD increases at other skeletal sites. The results of the intention-to-treat analysis were consistent with the primary analysis of completers.

14.2 Treatment to Increase Bone Mass in Men with Osteoporosis

The efficacy of alendronate sodium in men with hypogonadal or idiopathic osteoporosis was demonstrated in two clinical studies.

Daily Dosing

A two-year, double-blind, placebo-controlled, multicenter study of alendronate sodium 10 mg once daily enrolled a total of 241 men between the ages of 31 and 87 (mean, 63). All patients in the trial had either: 1) a BMD T-score less than or equal to -2 at the femoral neck and less than or equal to -1 at the lumbar spine, or 2) a baseline osteoporotic fracture and a BMD T-score less than or equal to -1 at the femoral neck. At two years, the mean increases relative to placebo in BMD in men receiving alendronate sodium 10 mg/day were significant at the following sites: lumbar spine, 5.3%; femoral neck, 2.6%; trochanter, 3.1%; and total body, 1.6%. Treatment with alendronate sodium also reduced height loss (alendronate, -0.6 mm vs. placebo, -2.4 mm).

Weekly dosing

A one-year, double-blind, placebo-controlled, multicenter study of once weekly alendronate sodium 70 mg enrolled a total of 167 men between the ages of 38 and 91 (mean, 66). Patients in the study had either: 1) a BMD T-score less than or equal to -2 at the femoral neck and less than or equal to -1 at the lumbar spine, 2) a BMD T-score less than or equal to -2 at the lumbar spine and less than or equal to -1 at the femoral neck, or 3) a baseline osteoporotic fracture and a BMD T-score less than or equal to -1 at the femoral neck. At one year, the mean increases relative to placebo in BMD in men receiving alendronate sodium 70 mg once weekly were significant at the following sites: lumbar spine, 2.8%; femoral neck, 1.9%; trochanter, 2.0%; and total body, 1.2%. These increases in BMD were similar to those seen at one year in the alendronate sodium 10 mg once-daily study.

In both studies, BMD responses were similar regardless of age (greater than or equal to 65 years vs. less than 65 years), gonadal function (baseline testosterone less than 9 ng/dL vs. greater than or equal to 9 ng/dL), or baseline BMD (femoral neck and lumbar spine T-score less than or equal to -2.5 vs. greater than -2.5).

16 HOW SUPPLIED/STORAGE AND HANDLING

BINOSTO effervescent tablets are round, flat faced, white to off-white tablets with beveled edges and "M" debossed on one side. BINOSTO effervescent tablets, 70 mg are provided in blisters made of aluminum foil composite, as follows:

NDC 70539-400-04 carton containing 4 units of use blisters

STORAGE AND HANDLING

Store at 20°C to 25°C (68°F to 77°F), excursions permitted to 15°C to 30°C (59°F to 86°F), [See USP Controlled Room Temperature.] Protect from moisture. Store tablets in original blister package until use.

17 PATIENT COUNSELING INFORMATION

See FDA-approved patient labeling (Medication Guide).

Instruct patients to read the Medication Guide before starting therapy with BINOSTO and to reread it each time the prescription is renewed.

17.1 Osteoporosis Recommendations, Including Calcium and Vitamin D Supplementation

Instruct patients to take supplemental calcium and vitamin D, if daily dietary intake is inadequate. Weight-bearing exercise should be considered along with the modification of certain behavioral factors, such as cigarette smoking and/or excessive alcohol consumption, if these factors exist.

17.2 Dosing Instructions

Instruct patients that it is necessary to follow all dosing instructions for BINOSTO:

- BINOSTO should only be taken upon arising for the day and must be taken at least 30 minutes before the first food, beverage, or medication of the day. Instruct patients not to attempt to swallow, chew, or suck on the tablet because of a potential for oropharyngeal ulceration.
- Instruct patients to dissolve the effervescent tablet in 4 ounces room temperature plain water only (not mineral water or flavored water).
- Instruct patients to wait at least 5 minutes after the effervescence stops and then stir the solution for approximately 10 seconds and then consume the contents.
- Instruct patients to avoid lying down for at least 30 minutes after taking BINOSTO and until after their first food of the day.
- Instruct patients not to take BINOSTO at bedtime or before arising for the day.
- Instruct patients that waiting less than 30 minutes, or taking BINOSTO with food, beverages (other than plain water) or other medications will lessen the effect of BINOSTO by decreasing its absorption into the body [see Drug Interactions (7.1)]. Even dosing with orange juice or coffee has been shown to markedly reduce the absorption of BINOSTO [see Clinical Pharmacology (12.3)].
- Inform patients that failure to follow these instructions may increase their risk of esophageal problems. [see Warnings and Precautions (5.1)].

Instruct patients that if they develop symptoms of esophageal disease (such as difficulty or pain upon swallowing, retrosternal pain or new or worsening heartburn) they should stop taking BINOSTO and consult their physician. [see Warnings and Precautions (5.1)].

Instruct patients that if they miss a dose of once weekly BINOSTO, they should take one dose on the morning after they remember. They should not take 2 doses on the same day but should return to taking one dose once a week, as originally scheduled on their chosen day.

17.3 Patients on Sodium Restriction

Inform patients who are prescribed sodium restricted diets that BINOSTO contains 603 mg of sodium which is equivalent to approximately 1532 mg NaCl per tablet.

Manufactured for:
Radius Health, Inc.
22 Boston Wharf Road, 7th Floor
Boston, MA 02210

US-PI-000400 – v2.0

MEDICATION GUIDE
BINOSTO® (BIN-oss-tow)
(alendronate sodium)
effervescent tablets for oral use

What is the most important information I should know about BINOSTO?
BINOSTO can cause serious side effects, including:

1. Esophagus problems
2. Low calcium levels in your blood (hypocalcemia)
3. Bone, joint, or muscle pain
4. Severe jaw bone problems (osteonecrosis)
5. Unusual breaks in thigh and other bones

1. Esophagus problems.
  Some people who take BINOSTO may develop problems in the esophagus (the tube that connects the mouth and the stomach). These problems include irritation, inflammation, or ulcers of the esophagus which may sometimes bleed.
  - It is important that you take BINOSTO exactly as prescribed to help lower your chance of getting esophagus problems. (See the section "How should I take BINOSTO?")
  - Stop taking BINOSTO and call your healthcare provider right away if you get chest pain, new or worsening heartburn, or have trouble or pain when you swallow.
2. Low calcium levels in your blood (hypocalcemia).
  BINOSTO may lower the calcium levels in your blood. If you have low blood calcium before you start taking BINOSTO, it may get worse during treatment. Your low blood calcium must be treated before you take BINOSTO. Most people with low blood calcium levels do not have symptoms, but some people may have symptoms. Call your healthcare provider right away if you have symptoms of low blood calcium such as:
  - Spasms, twitches, or cramps in your muscles
  - Numbness or tingling in your fingers, toes, or around your mouth
  Your healthcare provider may prescribe calcium and vitamin D to help prevent low calcium levels in your blood, while you take BINOSTO. Take calcium and vitamin D as your healthcare provider tells you to.
3. Bone, joint, or muscle pain.
  Some people who take BINOSTO develop severe bone, joint, or muscle pain.
4. Severe jaw bone problems (osteonecrosis).
  Severe jaw bone problems may happen when you take BINOSTO. Your healthcare provider should examine your mouth before you start BINOSTO. Your healthcare provider may tell you to see your dentist before you start BINOSTO. It is important for you to practice good mouth care during treatment with BINOSTO.
5. Unusual breaks in thigh and other bones.
  Some people have had unusual bone breaks, including thigh bone, when taking BINOSTO. A break in the thigh bone can feel like a new pain in your hip, groin, or thigh. People taking BINOSTO can also have breaks in other bones.

Call your healthcare provider right away if you have any of these side effects.

What is BINOSTO?
BINOSTO is a prescription medicine used to:

- Treat thinning of your bones (osteoporosis) in women after menopause. BINOSTO helps reduce the chance of having a hip or spinal fracture (break).
- Increase bone mass in men who have osteoporosis.

It is not known how long BINOSTO works for the treatment of osteoporosis. You should see your healthcare provider regularly to determine if BINOSTO is still right for you.
BINOSTO is not for use in children.

Who should not take BINOSTO?
Do not take BINOSTO if you:

- Have certain problems with your esophagus, the tube that connects your mouth with your stomach
- Cannot stand or sit upright for at least 30 minutes
- Have trouble swallowing liquids
- Have low levels of calcium in your blood
- Are allergic to BINOSTO or any of its ingredients. See the end of this leaflet for a complete list of ingredients in BINOSTO.

Before taking BINOSTO, tell your healthcare provider about all of your medical conditions, including if you:

- Have problems with swallowing
- Have stomach or digestive problems
- Have low blood calcium
- Plan to have dental surgery or teeth removed
- Have kidney problems
- Have been told you have trouble absorbing minerals in your stomach or intestines (malabsorption syndrome)
- Have been told to lower your salt intake
- Are pregnant, planning to become pregnant or suspect that you are pregnant. If you become pregnant while taking BINOSTO, stop taking it and contact your healthcare provider. It is not known if BINOSTO can harm your unborn baby.
- Are breastfeeding or plan to breastfeed. It is not known if BINOSTO passes into your milk and may harm your baby.

Tell your healthcare provider about all medicines you take, including prescription and non- prescription medicines, vitamins, and herbal supplements.
Especially tell your healthcare provider if you take:

- Calcium
- Antacids
- Aspirin
- Nonsteroidal Anti-Inflammatory (NSAID) medicines

Know the medicines you take. Keep a list of them and show it to your healthcare provider or pharmacist each time you get a new medicine.

How should I take BINOSTO?

- Take BINOSTO exactly as your healthcare provider tells you.
- BINOSTO is taken 1 time each week. Choose the day of the week that best fits your schedule, then take BINOSTO on the same day every week.
- BINOSTO works only if you take it on an empty stomach.
- Take BINOSTO after you get up for the day and 30 minutes before taking your first food, drink, or other medicine.
- Take BINOSTO while you are sitting or standing.
- Do not swallow, chew or suck on a BINOSTO tablet.
- Do not dissolve BINOSTO in:
  - Mineral or flavored water
  - Coffee
  - Tea
  - Soda
  - Juice
- You must dissolve your BINOSTO in plain water at room temperature before you take it. To prepare your BINOSTO liquid medicine:
  Step 1. Place the BINOSTO tablet in about a half glass (4 ounces) of plain water. The water should not be cold or hot, and should be at room temperature.
  Step 2. Wait at least 5 minutes after the bubbling (effervescence) stops for the BINOSTO tablet to completely dissolve in the water.
  Step 3. Stir the liquid medicine for about 10 seconds.
  Step 4. Drink all of the BINOSTO liquid medicine in the glass.

After you take BINOSTO, wait at least 30 minutes before you:

- Lie down. You may sit, stand or walk, and do normal activities like reading.
- Take your first food or drink, except for plain water.
- Take other medicines, including antacids, calcium, and other supplements and vitamins.

Do not lie down until after you eat your first food of the day.

- If you miss a dose of BINOSTO, do not take it later in the day. Take your missed dose on the next morning after you remember and then return to your normal schedule. Do not take 2 doses on the same day.
- If you think you took more than your prescribed dose of BINOSTO, drink a full glass of milk and call your healthcare provider right away. Do not try to vomit. Do not lie down.

What should I avoid while taking BINOSTO?
BINOSTO contains a high amount of salt in each tablet. Avoid eating foods with a high amount of salt if your healthcare provider has told you to limit how much salt you eat.

What are the possible side effects of BINOSTO?
BINOSTO may cause serious side effects.

- See "What is the most important information I should know about BINOSTO?"

The most common side effects of BINOSTO are:

- Stomach area (abdominal) pain
- Heartburn
- Constipation
- Diarrhea
- Upset stomach
- Pain in your bones, joints, or muscles
- Nausea

You may get allergic reactions, such as hives, swelling of your face, lips, tongue, or throat.
Tell your healthcare provider about any side effect that bothers you or that does not go away.
These are not all the side effects with BINOSTO. Ask your healthcare provider or pharmacist for more information.
Call your doctor for medical advice about side effects. You may report side effects to FDA at 1-800-FDA-1088.

How should I store BINOSTO?

- Store BINOSTO at room temperature between 68°F to 77°F (20°C to 25°C).
- Keep BINOSTO tablets in their original blister pack until you use them.
- Protect BINOSTO from moisture.
- Keep BINOSTO and all medicines out of the reach of children.

General information about the safe and effective use of BINOSTO.
Medicines are sometimes prescribed for purposes other than those listed in a Medication Guide. Do not use BINOSTO for a condition for which it was not prescribed. Do not give BINOSTO to other people, even if they have the same symptoms that you have. It may harm them.
You can ask your pharmacist or healthcare provider for information about BINOSTO that is written for health professionals.

What are the ingredients in BINOSTO?
Active ingredient: alendronate sodium
Inactive ingredients: monosodium citrate anhydrous, citric acid anhydrous, sodium hydrogen carbonate, sodium carbonate anhydrous, strawberry flavor, acesulfame potassium, and sucralose.
Radius Health, Inc., 22 Boston Wharf Road, 7th Floor, Boston, MA 02210
US-MG-000400-v2.0
For more information about BINOSTO, visit our website at www.BINOSTO.com or call Radius Health, Inc., at 1-855-672-3487.

This Medication Guide has been approved by the U.S. Food and Drug Administration.

Revised: 02/2026

PRINCIPAL DISPLAY PANEL - 4 Tablet Blister Pack

Fold and tear at
notch or cut

NDC 70539-400-00

Binosto®
(alendronate sodium) effervescent
tablet for oral solution
70 mg

Rx only

This blister contains 1 complete week of treatment

2023-BIN-0001

Manufactured for:
Radius Health, Inc.
22 Boston Wharf Road, 7th Floor
Boston, MA 02210 USA

PRINCIPAL DISPLAY PANEL - 4 Tablet Blister Pack Carton

NDC 70539-400-04
Rx only

Binosto®
(alendronate sodium) effervescent
tablet for oral solution
70 mg*

* Each effervescent tablet contains 91.37 mg
alendronate sodium (70 mg free acid equivalent)

4 Effervescent Tablets

ATTENTION PHARMACIST:
Each patient is required to
receive the medication guide.

PRINCIPAL DISPLAY PANEL - 4 Tablet Blister Sample Pack Carton

NDC 70539-400-94
Rx only

SAMPLE—NOT FOR SALE

Binosto®
(alendronate sodium) effervescent
tablet for oral solution
70 mg*

* Each effervescent tablet contains 91.37 mg
alendronate sodium (70 mg free acid equivalent)

4 Effervescent Tablets

ATTENTION PHARMACIST:
Each patient is required to
receive the medication guide.